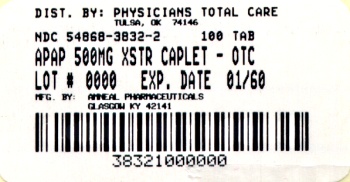 DRUG LABEL: Acetaminophen
NDC: 54868-3832 | Form: TABLET
Manufacturer: Physicians Total Care, Inc.
Category: otc | Type: HUMAN OTC DRUG LABEL
Date: 20120924

ACTIVE INGREDIENTS: ACETAMINOPHEN 500 mg/1 1
INACTIVE INGREDIENTS: POVIDONE; STARCH, CORN; SODIUM STARCH GLYCOLATE TYPE A POTATO; STEARIC ACID

Acetaminophen Tablets
Extra Strength

*Compared to the active ingredient in Extra Strength Tylenol®

Drug Facts

ACTIVE INGREDIENT

(in each tablet)

Acetaminophen 500 mg

PURPOSES

Pain Reliever/Fever Reducer

USES

For the temporary relief of minor aches and pains due to:

- Headache
- Muscular aches
- Backache
- Minor pain of arthritis
- The common cold
- Toothache
- Premenstrual and menstrual cramps

Temporarily reduces fever.

WARNINGS

Liver warning:

This product contains acetaminophen. Severe liver damage may occur if you take

- more than 8 caplets in 24 hours, which is the maximum daily amount
- with other drugs containing acetaminophen
- 3 or more alcoholic drinks every day while using this product

Do not use

- with any other drug containing acetaminophen (prescription or nonprescription). If you are not sure whether a drug contains acetaminophen, ask a doctor or pharmacist.
- if you are allergic to acetaminophen or any of the inactive ingredients in this product

Ask a doctor before use if you have liver disease.

Ask a doctor or pharmacist before use if you are taking the blood thinning drug warfarin.

Stop use and ask a doctor if

- Pain gets worse or lasts more than 10 days
- Fever gets worse or lasts more than 3 days
- New symptoms occur
- Redness or swelling is present

These could be signs of a serious condition.

If pregnant or breast-feeding, ask a health professional before use.

Keep out of reach of children.

Overdose warning

Taking more than the recommended dose (overdose) may cause liver damage. In the case of overdose, get medical help or contact a Poison Control Center right away. (1-800-222-1222). Quick medical attention is critical for adults as well as for children even if you do not notice any signs or symptoms.

DIRECTIONS

Do not take more than directed.

Adults and children 12 years and over:

- Take 2 caplets every 4 to 6 hours while symptoms last
- Do not take more than 8 caplets in 24 hours
- Do not take for more than 10 days unless directed by a doctor

Children under 12 years:

- Do not use adult Extra Strength product in children under 12 years of age; this will provide more than the recommended dose (overdose) of acetaminophen and may cause liver damage.

OTHER INFORMATION

- Store at room temperature 15°-30°C (59°-86°F)
- Use by expiration date on package

INACTIVE INGREDEINTS

Povidone, Pregelatinized Starch, Sodium Starch Glycolate, Stearic Acid

Questions? To report a Serious Adverse Event contact 1-877-835-5472.

*This product is not manufactured or distributed by McNeil Consumer Products Co., owners of the registered trademark Tylenol®.

Distributed by:

Amneal Pharmaceuticals

104 Hippocrates Way,

Glasgow, KY 42141

Rev. 11/2009

Additional barcode labeling by:
Physicians Total Care, Inc.
Tulsa, Oklahoma 74146

PACKAGE LABEL.PRINCIPAL DISPLAY PANEL

Acetaminophen
Caplets
Extra Strength
500 mg
NDC 54868-3832-1

Keep out of reach of children.